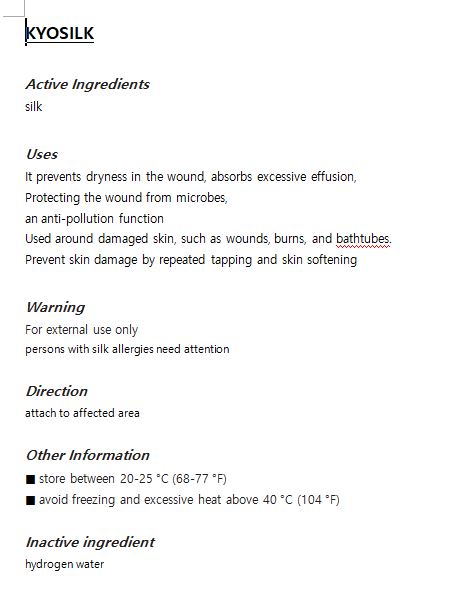 DRUG LABEL: KYOSILK
NDC: 73353-0001 | Form: LIQUID
Manufacturer: TOYOWADO SILKTECH CO., LTD
Category: otc | Type: HUMAN OTC DRUG LABEL
Date: 20190915

ACTIVE INGREDIENTS: SILK SERICIN 40 g/100 mL
INACTIVE INGREDIENTS: WATER

Drug Facts

ACTIVE INGREDIENT

silk

INACTIVE INGREDIENT

hydrogen water

PURPOSE

It prevents dryness in the wound, absorbs excessive effusion,

Protecting the wound from microbes,

an anti-pollution function

Used around damaged skin, such as wounds, burns, and bathtubes.

Prevent skin damage by repeated tapping and skin softening by extrusion.

keep out of reach of the children

INDICATIONS AND USAGE

attach to the affected part

WARNINGS

Persons with silk allergies need attention

DOSAGE AND ADMINISTRATION

for external use only